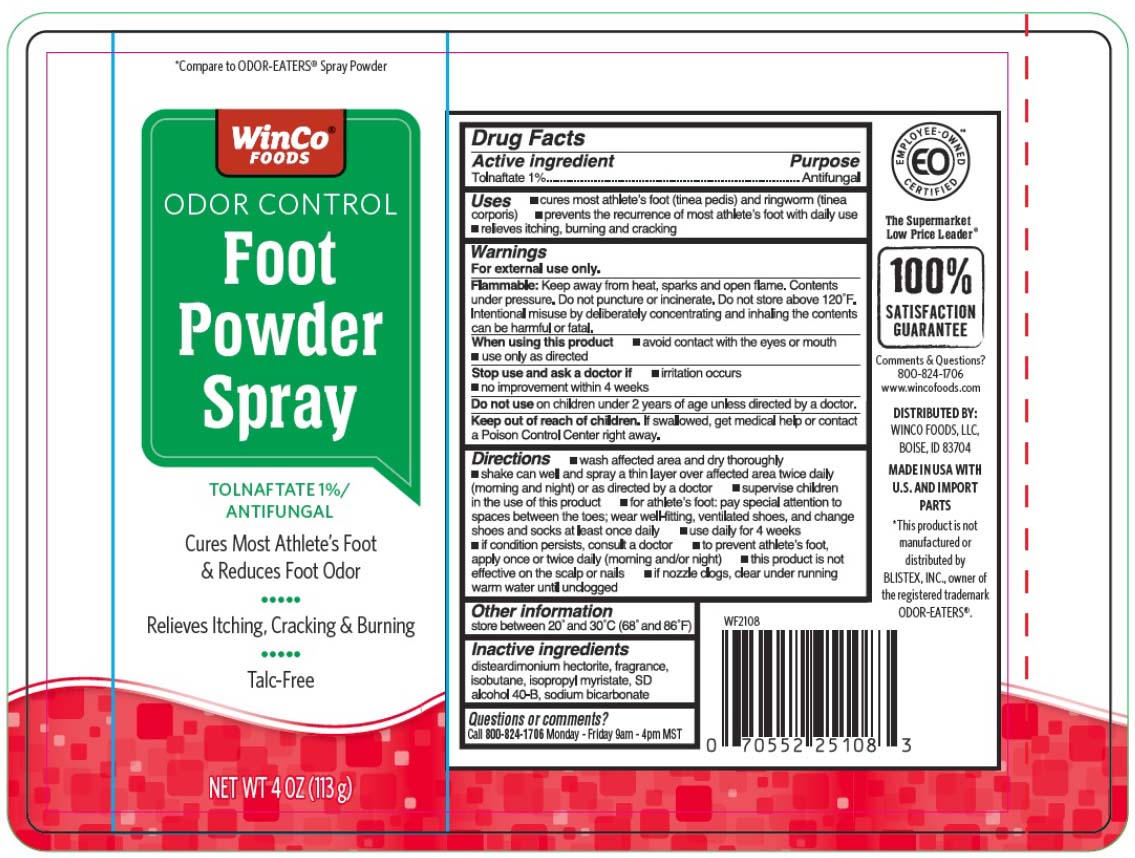 DRUG LABEL: Tolnaftate
NDC: 67091-390 | Form: AEROSOL, SPRAY
Manufacturer: Winco Foods, LLC
Category: otc | Type: HUMAN OTC DRUG LABEL
Date: 20251216

ACTIVE INGREDIENTS: TOLNAFTATE 1.3 g/113 g
INACTIVE INGREDIENTS: DISTEARDIMONIUM HECTORITE; ISOBUTANE; ALCOHOL; SODIUM BICARBONATE; ISOPROPYL MYRISTATE

Winco Foot Odor Control Powder Spray

Active ingredient

Tolnaftate 1%

Purpose

Antifungal

Uses

- cures mose athlete's foot (tinea pedis) and ringworm (tinea corporis)
- prevents recurrence of athlete's foot with daily use
- relieves itching, burning and cracking

Warnings

For external use only.

Flammable:

Keep away from heat, sparks and open flame. Contents under pressure. Do not puncture or incinerate. Do not store above 120°F. Intentional misuse by deliberately concentrating and inhaling the contents cans be harmful or fatal.

When using this product

- avoid contact with the eyes or mouth
- use only as directed

Stop use and ask a doctor if

- irritation occurs
- no improvement within 4 weeks

Do not use

on children under 2 years of age unless directed by a doctor.

Keep out of reach of children.

If swallowed, get medical help or contact a Poison Control Center right away.

Directions

- wash affected area and dry thoroughly
- shake can well and spray a thin layer over affected area twice daily (morning and night) or as directed by a doctor
- supervise children in the use of this product
- for athlete's foot: pay special attention to spaces between the toes; wear well-fitting, ventilated shoes, and change shoes and socks at least once daily
- use daily for 4 weeks
- if conditions persists, consult a doctor
- to prevent athlete's foot, apply once or twice daily (morning and/or night)
- this product is not effective on the scalp or nails
- if nozzle clogs, clear nozzle under running warm water until unclogged

Other information

store between 20º and 30ºC (68º and 86ºF)

Inactive ingredients

disteardimonium hectorite, fragrance, isobutane, isopropyl myristate, SD alcohol 40-B, sodium bicarbonate

Questions?

Call 800-824-1706 Monday - Friday 9am - 4pm MST

Principal Display Panel

Odor Control

Foot

Powder

Spray

TOLNAFTATE 1%/

ANTIFUNGAL

Cures Most Athlete's Foot

& Reduces Foot Odor

Relieves Itching, Cracking & Burning

Talc-Free

NET WT 4 OZ (113g)